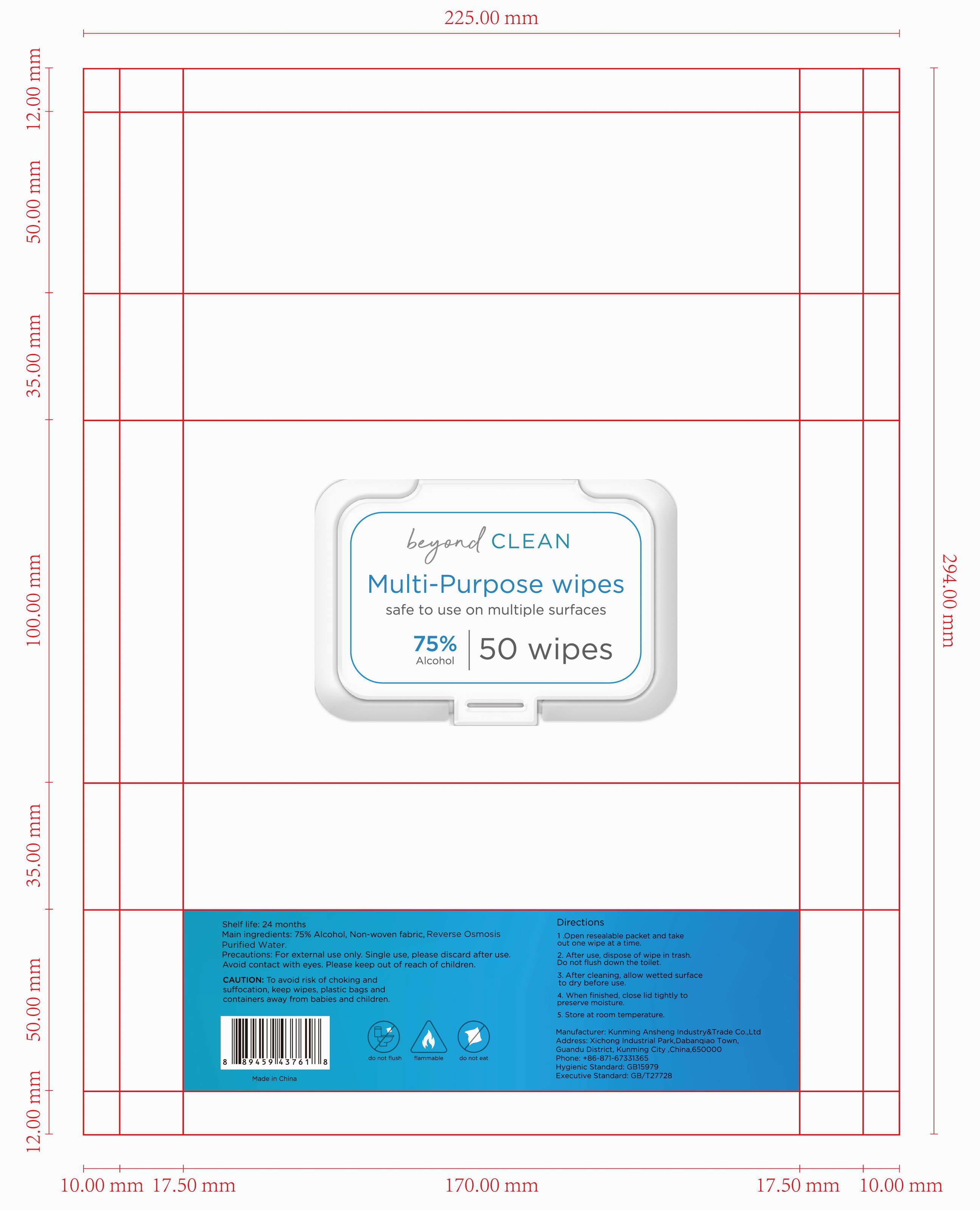 DRUG LABEL: Antibacterial Wet Wipes
NDC: 78183-009 | Form: CLOTH
Manufacturer: Kunming Ansheng Industry & Trade Co., Ltd.
Category: otc | Type: HUMAN OTC DRUG LABEL
Date: 20200801

ACTIVE INGREDIENTS: ALCOHOL 0.75 U/1 U
INACTIVE INGREDIENTS: WATER 0.25 U/1 U

Antibacterial Wet Wipes (beyond)

Active Ingredient(s)

Alcohol 75% v/v.

Purpose

Antibacterial;

Use

Safe to use on multiple surfaces.

Warnings

For external use only. Flammable. Do not flush. Do not eat. Single use, please discard after use.

Do not use

To avoid risk of choking and suffocation, keep wipes, plastic bags and containers away from babies and children.

WHEN USING

Avoid contact with eyes.

Stop use and ask a doctor if irritation or rash appears and lasts.

Please keep out of reach of children.

Directions

1. Open resealable packet and take out one wipe at a time.
2. After use, dispose of wipe in trash. Do not flush down the toilet.
3. After cleaning, allow wetted surface to dry before use.
4. When finished, close lid tightly to preserve moisture.
5. Store at room temperature.

Inactive ingredients

Pure water

Package Label - Principal Display Panel

50 wipes in 1 BAG;

NDC: 78183-009-01.